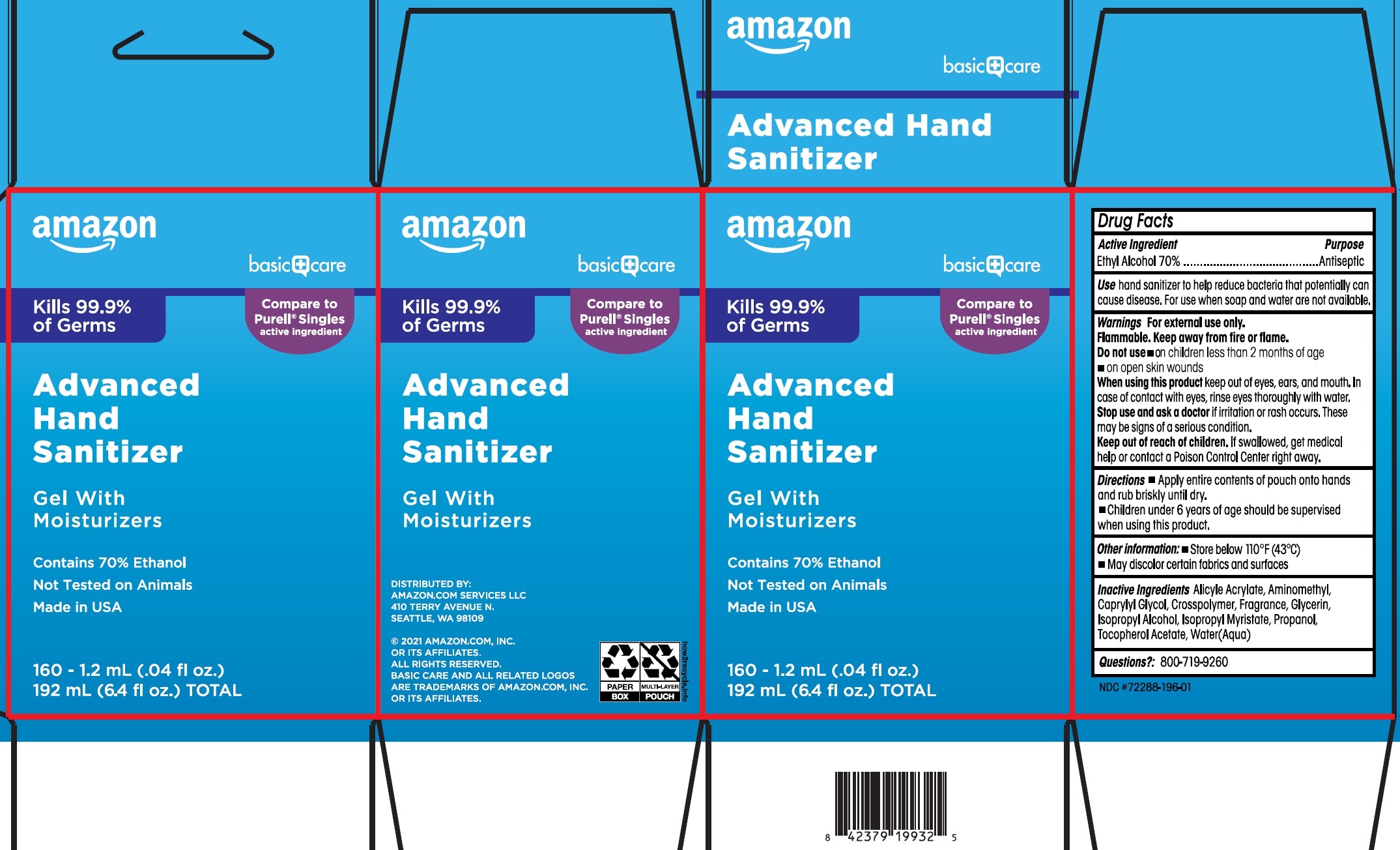 DRUG LABEL: Hand Sanitizer
NDC: 72288-196 | Form: GEL
Manufacturer: Amazon Services LLC
Category: otc | Type: HUMAN OTC DRUG LABEL
Date: 20250224

ACTIVE INGREDIENTS: ALCOHOL 70 mL/100 mL
INACTIVE INGREDIENTS: CAPRYLYL GLYCOL; GLYCERIN; ISOPROPYL ALCOHOL; ISOPROPYL MYRISTATE; PROPYL ALCOHOL; .ALPHA.-TOCOPHEROL ACETATE; WATER

Amazon Advanced Hand Sanitizer

Active Ingredient

Ethyl Alcohol 70%

Purpose

Antiseptic

Use

hand sanitizer to help reduce bacteria that potentially can cause disease. For use when soap and water are not available.

Warnings

For external use only.

Flammable. Keep away from fire or flame.

Do not use

- on children less than 2 months of age
- on open skin wounds

When using this product

keep out of eyes, ears, and mouth. In case of contact with eyes, rinse eyes thoroughly with water.

Stop use and ask a doctor

if irritation or rash occurs. These may be signs of a serious condition.

Keep out of reach of children.

If swallowed, get medical help or contact a Poison Control Center right away.

Directions

- Apply entire contents of pouch onto hands and rub briskly until dry.
- Children under 6 years of age should be supervised when using this product.

Other information:

- Store below 110°F (43°C)
- May discolor certain fabrics and surfaces

Inactive Ingredients

Alicyle Acrylate, Aminomethyl, Caprylyl Glycol, Crosspolymer, Fragrance, Glycerin, Isopropyl Alcohol, Isopropyl Myristate, Propanol, Tocopherol Acetate, Water(Aqua)

Questions?:

800-719-9260